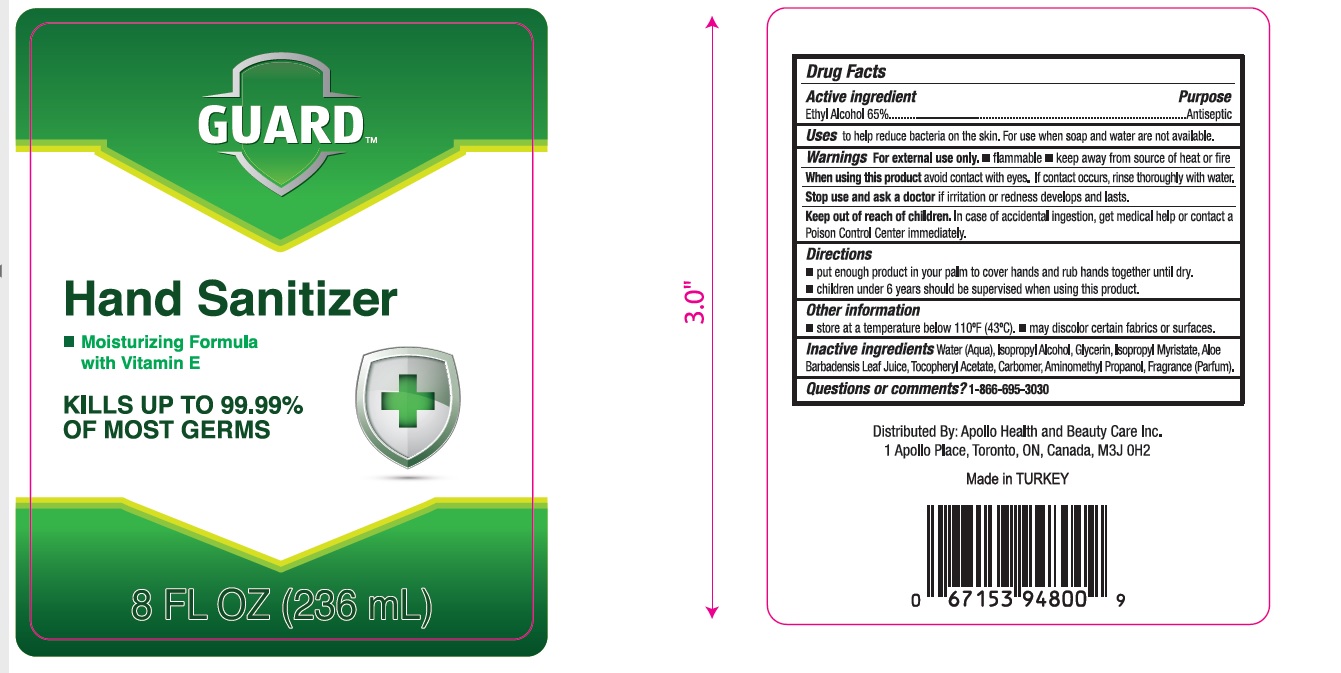 DRUG LABEL: Guard Hand Sanitizer
NDC: 76772-000 | Form: GEL
Manufacturer: TSM ITHALAT IHRACAT SANAYI VE DIS TICARET LIMITED SIRKETI
Category: otc | Type: HUMAN OTC DRUG LABEL
Date: 20200703

ACTIVE INGREDIENTS: ALCOHOL 0.65 mL/1 mL
INACTIVE INGREDIENTS: WATER; ISOPROPYL ALCOHOL; ALOE VERA LEAF; PROPYLENE GLYCOL; GLYCERIN; CARBOMER COPOLYMER TYPE A; .ALPHA.-TOCOPHEROL ACETATE, D-; AMINOMETHYLPROPANOL; ISOPROPYL MYRISTATE

Guard Hand Sanitizer

Active Ingredients

Ethyl Alcohol 65%

Purpose: Antiseptic

Purpose

Antiseptic

Safety Instructions

Flammable, Keep away from fire and flame

Ask Doctor

Stop Use and Ask a doctor if irritation or redness develops

KEEP OUT OF REACH OF CHILDREN

If swallowed, get medical help or contact Poison Control right away

Other Information

Store below 110°F (43°C)
May discolor certain fabrics or surfaces.

Inactive Ingredients

water, isopropyl alcohol, glycerin, carbomer, aminomethyl propanol, fragrance, propylene glycol, aloe, tocopheryl acetate, isopropyl myristate

Directions

- Place enough product in your palm to thoroughly cover your hands
- Rub hands together briskly until dry
- Children under 6 years of age should be supervised when using this product.

Warnings

For external use only.

Flammable. Keep away from fire or flame.

Uses

- helps reduce bacteria on the skin that could cause disease
- Recommended for repeated use